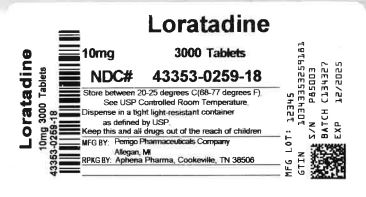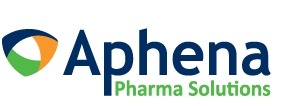 DRUG LABEL: Loratadine
NDC: 43353-259 | Form: TABLET
Manufacturer: Aphena Pharma Solutions - Tennessee, LLC
Category: otc | Type: HUMAN OTC DRUG LABEL
Date: 20240409

ACTIVE INGREDIENTS: LORATADINE 10 mg/1 1
INACTIVE INGREDIENTS: LACTOSE MONOHYDRATE; MAGNESIUM STEARATE; POVIDONE, UNSPECIFIED

Perrigo Loratadine Tablets, 10 mg Drug Facts

Active ingredient (in each tablet)

Loratadine 10 mg

Purpose

Antihistamine

Uses

temporarily relieves these symptoms due to hay fever or other upper respiratory allergies:

- runny nose
- itchy, watery eyes
- sneezing
- itching of the nose or throat

Warnings

Do not use

if you have ever had an allergic reaction to this product or any of its ingredients

Ask a doctor before use if you have

liver or kidney disease. Your doctor should determine if you need a different dose.

When using this product

do not take more than directed. Taking more than directed may cause drowsiness.

Stop use and ask a doctor if

an allergic reaction to this product occurs. Seek medical help right away.

If pregnant or breast-feeding,

ask a health professional before use.

Keep out of reach of children.

In case of overdose, get medical help or contact a Poison Control Center right away. (1-800-222-1222)

Directions

adults and children 6 years and over | 1 tablet daily; not more than 1 tablet in 24 hours
children under 6 years of age | ask a doctor
consumers with liver or kidney disease | ask a doctor

Other information

- do not use if printed foil under cap is broken or missing
- store between 20° to 25°C (68° to 77°F)

Inactive ingredients

lactose monohydrate, magnesium stearate, povidone, pregelatinized starch

Questions or comments?

1-800-719-9260

Repackaging Information

Please reference the HOW SUPPLIED section listed above for a description of individual drug products listed below. This drug product has been received by Aphena Pharma Solutions - Tennessee, LLC in a manufacturer or distributor packaged configuration and repackaged in full compliance with all applicable cGMP regulations. The package configurations available from Aphena are listed below:

10mg
NDC 43353-259-60, Bottles of 90 Tablets
NDC 43353-259-18, Bottles of 3000 Tablets
NDC 43353-259-09, Bottles of 9000 Tablets

Store between 20°-25°C (68°-77°F). See USP Controlled Room Temperature. Dispense in a tight light-resistant container as defined by USP. Keep this and all drugs out of the reach of children.

Repackaged by:
Cookeville, TN 38506
20240409AMH

PRINCIPAL DISPLAY PANEL - 10 mg

NDC 43353-259 - Loratadine 10 mg Tablets